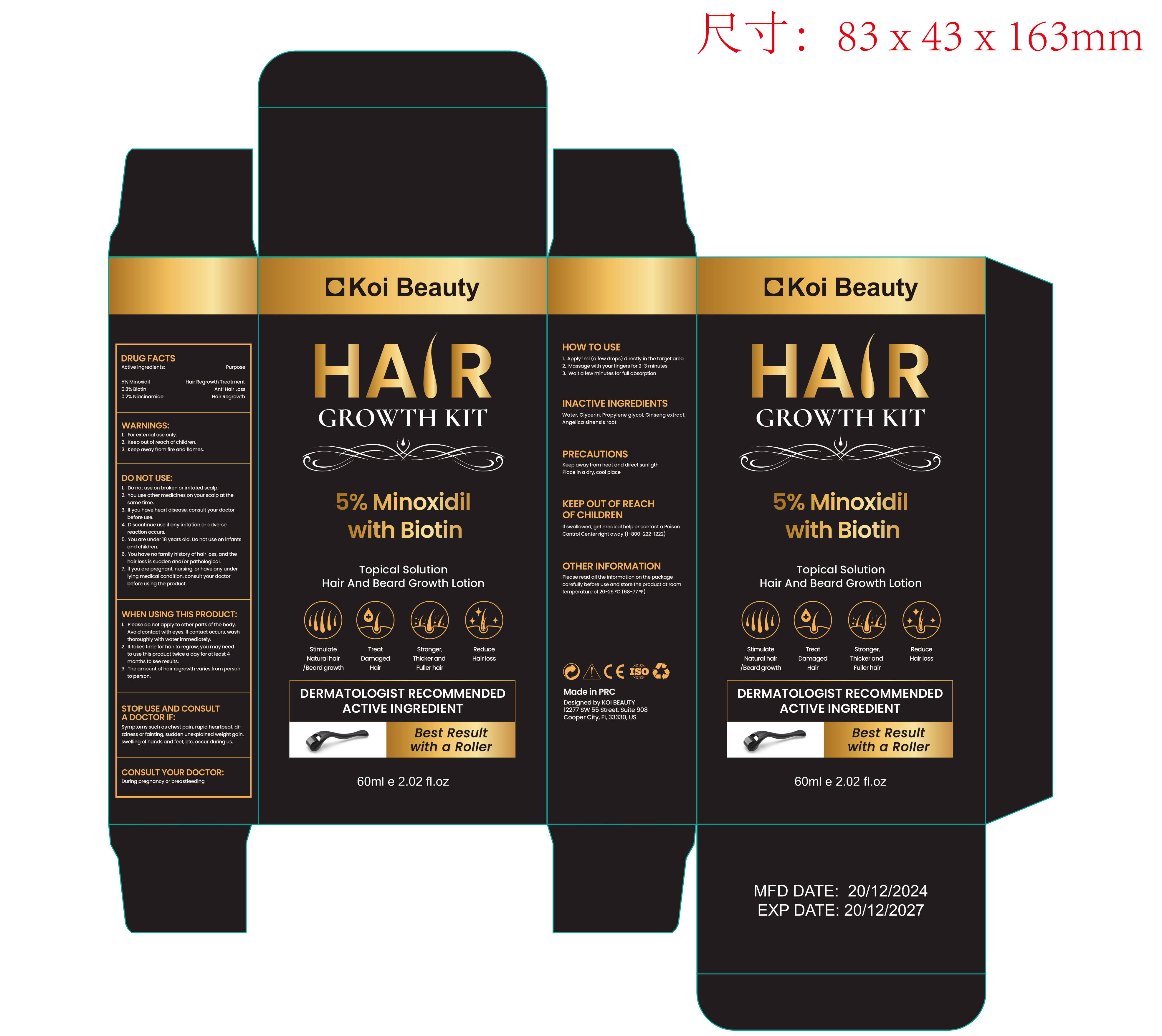 DRUG LABEL: Koi Beauty 5% Minoxidil Hair Growth Kit
NDC: 85709-002 | Form: LIQUID
Manufacturer: Beijing Sea Heart International Science And Technology Co.,Ltd.
Category: otc | Type: HUMAN OTC DRUG LABEL
Date: 20250731

ACTIVE INGREDIENTS: MINOXIDIL 5 mg/100 mL; NIACINAMIDE 0.2 mg/100 mL; BIOTIN 0.3 mg/100 mL
INACTIVE INGREDIENTS: ANGELICA SINENSIS ROOT; PROPYLENE GLYCOL; GLYCERIN; PANAX GINSENG ROOT; WATER

Koi Beauty 5% Minoxidil Hair Growth Kit

ACTIVE INGREDIENT

5% Minoxidil

0.3% Biotin

0.2% Niacinamide

PURPOSE

Hair Regrowth Treatment

WARNINGS:

1.For external use only.

2.Keep out of reach of children.

3.Keep away from fire and flames.

DO NOT USE:

1. Do not use on broken or irritated scalp.

2. You use other medicines on your scalp at the same time.

3. If you have heart disease, consult your doctor before use.

4. Discontinue use if any irritation or adverse reaction occurs.

5. You are under 18 years old. Do not use on infants and children.

6. You have no family history of hair loss, and the hair loss is sudden and/or pathological.

7. If you are pregnant, nursing, or have any under lying medical condition, consult your doctor before using the product.

WHEN USING THIS PRODUCT:

1. Please do not apply to other parts of the body. Avoid contact with eyes. If contact occurs, wash thoroughly with water immediately.

2. It takes time for hair to regrow , you may need to use this product twice a day for at least 4 months to see results.

3. The amount of hair regrowth varies from person to person.

STOP USE AND CONSULT A DOCTOR IF:

Symptoms such as chest pain, rapid heartbeat, dizziness or fainting, sudden unexplained weight gain, swelling of hands and feet, etc. occur during use.

CONSULT YOUR DOCTOR:

During pregnancy or breastfeeding

DOSAGE AND ADMINISTRATION

HOW TO USE

1. Apply 1ml (a few drops) directly in the target area

2. Massage with your fingers for 2-3 minutes

3. Wait a few minutes for full absorption

INACTIVE INGREDIENTS

Water, Glycerin, Propylene glycol, Ginseng extract, Angelica sinensis root

INDICATIONS AND USAGE

HOW TO USE

1. Apply 1ml (a few drops) directly in the target area

2. Massage with your fingers for 2-3 minutes

3. Wait a few minutes for full absorption

PRECAUTIONS

Keep away from heat and direct sunlight

Place in a dry, cool place

KEEP OUT OF REACH OF CHILDREN

If swallowed, get medical help or contact a Poison Control Center right away (1-800-222-1222)

OTHER INFORMATION

Please read all the information on the package carefully before use and store the product at room temperature of 20-25 ℃ (68-77 ℉)